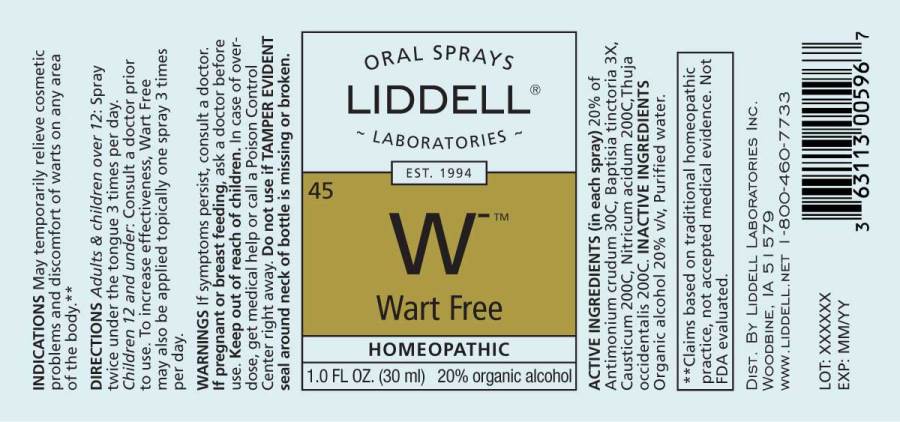 DRUG LABEL: Wart Free
NDC: 50845-0057 | Form: SPRAY
Manufacturer: Liddell Laboratories, Inc.
Category: homeopathic | Type: HUMAN OTC DRUG LABEL
Date: 20181105

ACTIVE INGREDIENTS: ANTIMONY TRISULFIDE 30 [hp_C]/1 mL; BAPTISIA TINCTORIA ROOT 3 [hp_X]/1 mL; CAUSTICUM 200 [hp_C]/1 mL; NITRIC ACID 200 [hp_C]/1 mL; THUJA OCCIDENTALIS LEAFY TWIG 200 [hp_C]/1 mL
INACTIVE INGREDIENTS: WATER; ALCOHOL

Drug Facts

ACTIVE INGREDIENTS:

(in each spray): 20% of Antimonium crudum 30C, Baptisia tinctoria 3X, Causticum 200C, Nitricum acidum 200C, Thuja occidentalis 200C.

INDICATIONS:

May temporarily relieve cosmetic problems and discomfort of warts on any area of the body.**

**Claims based on traditional homeopathic practice, not accepted medical evidence. Not FDA evaluated.

WARNINGS:

If symptoms persist, consult a doctor.

If pregnant or breast feeding, ask a doctor before use.

Keep out of reach of children. In case of overdose, get medical help or call a Poison Control Center right away.

Do not use if TAMPER EVIDENT seal around neck of bottle is missing or broken.

DIRECTIONS:

Adults and children over 12: Spray twice under the tongue 3 times per day. Children 12 and under: Consult a doctor prior to use.

Wart Free can also be applied topically one spray 3 times per day to increase effectiveness.

INACTIVE INGREDIENTS:

Organic alcohol 20% v/v, Purified water.

Keep out of reach of children. In case of overdose, get medical help or call a Poison Control Center right away.

INDICATIONS:

May temporarily relieve cosmetic problems and discomfort of warts on any area of the body.**

**Claims based on traditional homeopathic practice, not accepted medical evidence. Not FDA evaluated.

QUESTIONS:

DIST. BY LIDDELL LABORATORIES INC.

WOODBINE, IA 51579

WWW.LIDDELL.NET 1-800-460-7733

PACKAGE LABEL DISPLAY:

ORAL SPRAYS

LIDDELL

LABORATORIES
EST. 1994
^45 W^-
Wart Free
HOMEOPATHIC
1.0 FL. OZ. (30 ml)